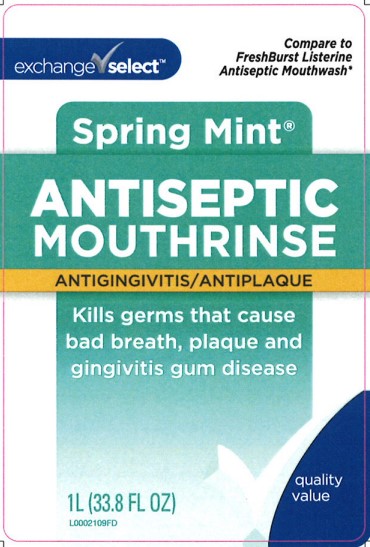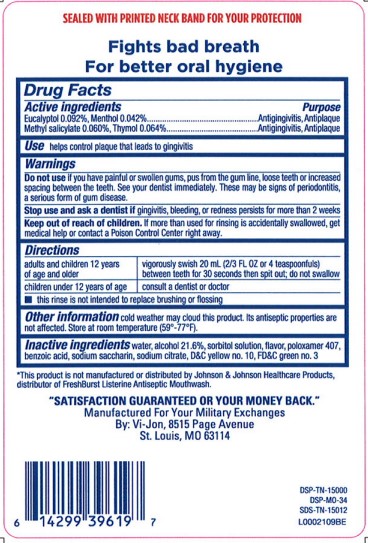 DRUG LABEL: Antiseptic Mouth Rinse
NDC: 55301-072 | Form: MOUTHWASH
Manufacturer: Your Military Exchanges
Category: otc | Type: HUMAN OTC DRUG LABEL
Date: 20260212

ACTIVE INGREDIENTS: EUCALYPTOL 0.92 mg/1 mL; MENTHOL 0.42 mg/1 mL; METHYL SALICYLATE 0.6 mg/1 mL; THYMOL 0.64 mg/1 mL
INACTIVE INGREDIENTS: WATER; ALCOHOL; SORBITOL; POLOXAMER 407; BENZOIC ACID; SACCHARIN SODIUM; SODIUM CITRATE; D&C YELLOW NO. 10; FD&C GREEN NO. 3

Exchange Select 072.003 072AL rev 2 072AN
Spring Mint Antiseptic Mouthrinse

TEP

SEALED WITH PRINTED NECK BAND FOR YOUR PROTECTION

CLAIMS

Fights bad breath

For better oral hygiene

Active ingredients

Eucalytpol 0.092%, Menthol 0.042%

Methyl salicylate 0.060% Thymol 0.064%

Purpose

Antigingivitis, Antiplaque

Use

helps control plaque that leads to gingivitis

Warnings

For this product

Do not use

if you have painful or swollen gums, pus from the gum line, loose teeth or increased spacing between teeth. See your dentist immediately. These may be signs of periodontitis, a serious form of gum disease.

Stop use and ask a dentist if

gingivitis, bleeding, or redness persists for more than 2 weeks

Keep out of reach of children

If more than used for rinsing is accidentally swallowed, get medical help or contact a Poison Control Center right away.

Directions

Adults and children 12 years of age and older - vigorously swish 20 mL (2/3 FL OZ or 4 teaspoonfuls) between teeth for 30 seconds then spit out; do not swallow

children under 12 years of age - consult a dentist or doctor

- this rinse is not intended to replace brushing or flossing

STORAGE AND HANDLING

cold weather may cloud those product. Its antiseptic properties are not affected. Store at room temperature (59⁰ -77⁰ F)

Inactive ingredients

water, alcohol 21.6%, sorbitol solution, flavor, poloxamer 407, benzoic acid, sodium saccharin, sodium citrate, D&C Yellow no.10, FD&C green no.3

Disclaimer

*This product is not manufactured or distributed by Johnson & Johnson Healthcare Products, distributor of FreshBurst Listerine Antiseptic Mouthwash.

Adverse reactions section

"SATISFACTON GUARANTEED OR YOUR MONEY BACK."

Manufactured For Your Military Exchanges

By: Vi-Jon, 8515 Page Avenue

St. Louis, MO 63114

DSP-TN-15000

DSP-MO-34

SDS-TN-15012

principal display panel

exchange select™

Compare to FreshBurst Listerine Antiseptic Mouthwash*

Spring Mint ®

ANTISEPTIC MOUTHRINSE

ANTIGINGIVITIS/ANTIPLAQUE

Kills germs that cause bad breath, plaque and gingivitis gum disease

quaity value

1 L (33.8 FL OZ)